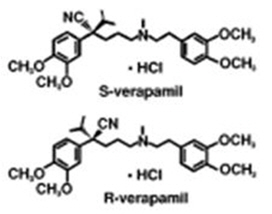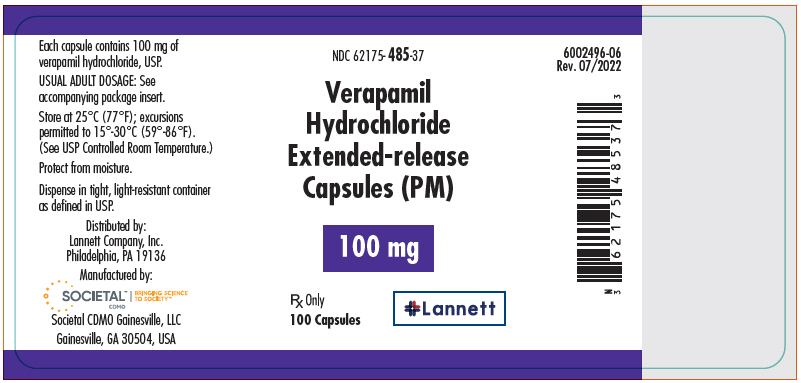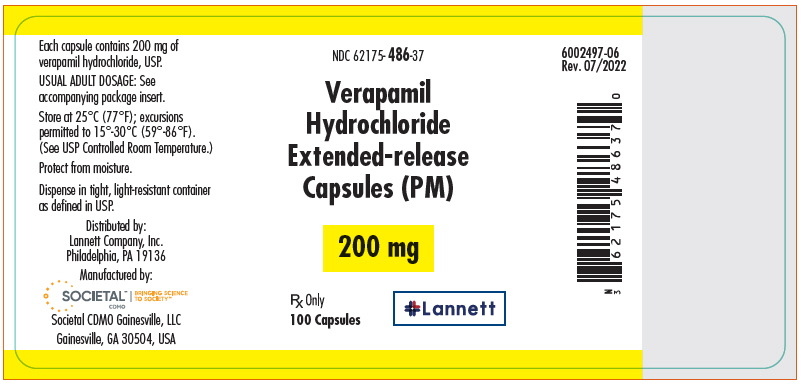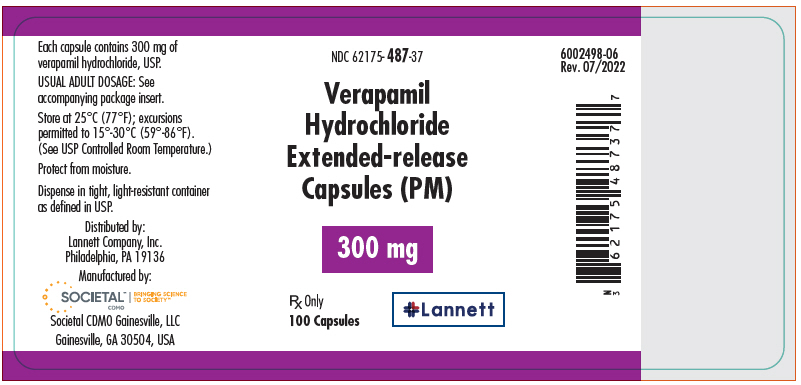 DRUG LABEL: Verapamil Hydrochloride
NDC: 62175-485 | Form: CAPSULE, EXTENDED RELEASE
Manufacturer: Lannett Company, Inc.
Category: prescription | Type: HUMAN PRESCRIPTION DRUG LABEL
Date: 20221227

ACTIVE INGREDIENTS: VERAPAMIL HYDROCHLORIDE 100 mg/1 1
INACTIVE INGREDIENTS: D&C RED NO. 28; FD&C BLUE NO. 1; FD&C RED NO. 40; FUMARIC ACID; GELATIN, UNSPECIFIED; POVIDONE, UNSPECIFIED; SHELLAC; SILICON DIOXIDE; SODIUM LAURYL SULFATE; STARCH, CORN; SUCROSE; TALC; TITANIUM DIOXIDE

HIGHLIGHTS OF PRESCRIBING INFORMATION

These highlights do not include all the information needed to use VERAPAMIL HYDROCHLORIDE EXTENDED-RELEASE CAPSULES (PM) safely and effectively. See full prescribing information for VERAPAMIL HYDROCHLORIDE EXTENDED-RELEASE CAPSULES (PM).
Verapamil Hydrochloride Extended-release Capsules (PM) for oral use
Initial U.S. Approval: 1998

1 INDICATIONS AND USAGE

Verapamil Hydrochloride Extended-release Capsules (PM) is a calcium channel blocker indicated for the treatment of hypertension, to lower blood pressure. Lowering blood pressure reduces the risk of fatal and nonfatal cardiovascular events, primarily strokes and myocardial infarctions. (1)

2 DOSAGE AND ADMINISTRATION

- Do not crush or chew capsule contents; swallow capsule whole or sprinkle entire contents onto applesauce (2.2, 17)
- Usual dosage: 200 mg once daily at bedtime; if inadequate response, titrate upward to 300 mg, then 400 mg once daily at bedtime (2.1)
- Initial dose of 100 mg once daily at bedtime in patients with renal or hepatic impairment, elderly or low-weight patients (2.1)

3 DOSAGE FORMS AND STRENGTHS

Extended-release capsules controlled-onset: 100 mg, 200 mg, and 300 mg (3)

4 CONTRAINDICATIONS

- Severe left ventricular dysfunction (4)
- Hypotension (<90 mmHg systolic pressure) or cardiogenic shock (4)
- Sick sinus syndrome (except in patients with pacemaker) (4)
- 2nd- or 3rd-degree AV block (except in patients with pacemaker) (4)
- Atrial flutter or atrial fibrillation and an accessory bypass tract (4)

5 WARNINGS AND PRECAUTIONS

- Congestive heart failure or pulmonary edema may develop (5.1)
- Hypotension/dizziness may occur (5.2)
- Elevated transaminases have occurred; monitor liver function (5.3)
- Ventricular fibrillation has occurred in patients with atrial flutter or atrial fibrillation and an accessory bypass tract (5.4)
- Reduce dose or discontinue therapy if marked first-degree AV block or progression to second- or third-degree AV block occurs (5.5)
- Sinus bradycardia, pulmonary edema, severe hypotension, second-degree AV block, sinus arrest, and death occurred in patients with hypertrophic cardiomyopathy (5.6)

6 ADVERSE REACTIONS

Most common adverse reactions (incidence ≥ 3% and more common than in patients treated with placebo) are headache, infection, constipation, flu syndrome, peripheral edema, dizziness, pharyngitis, and sinusitis (6.1)

To report SUSPECTED ADVERSE REACTIONS, contact Lannett Company, Inc. at 1-844-834-0530 or FDA at 1-800-FDA-1088 or www.fda.gov/medwatch.

7 DRUG INTERACTIONS

- CYP3A4 inhibitors increase verapamil levels (7.1)
- CYP3A4 inducers decrease verapamil levels (7.1)
- If simvastatin is co-administered with verapamil, do not exceed doses greater than 10 mg daily of simvastatin (7.2)
- If lovastatin is co-administered with verapamil, do not exceed doses greater than 40 mg daily of lovastatin (7.2)
- Grapefruit juice may significantly increase verapamil levels (7.3)
- Beta blockers: reports of excess bradycardia and AV block, including complete heart block; monitor closely (7.4)
- Digoxin levels can increase by 50 to 75%; reduce digoxin dose (7.5)
- Alcohol elimination inhibited resulting in elevated ethanol levels (7.6)

8 USE IN SPECIFIC POPULATIONS

- Use during pregnancy only if potential benefit justifies the potential risk to the fetus (8.1)
- Discontinue nursing while verapamil is administered (8.3)
- Safety and effectiveness in pediatric patients have not been established (8.4)

FULL PRESCRIBING INFORMATION

1 INDICATIONS AND USAGE

Verapamil Hydrochloride Extended-release Capsules (PM) for oral use is indicated for the treatment of hypertension, to lower blood pressure. Lowering blood pressure reduces the risk of fatal and nonfatal cardiovascular events, primarily strokes and myocardial infarctions. These benefits have been seen in controlled trials of antihypertensive drugs from a wide variety of pharmacologic classes including this drug.

Control of high blood pressure should be part of comprehensive cardiovascular risk management, including, as appropriate, lipid control, diabetes management, antithrombotic therapy, smoking cessation, exercise, and limited sodium intake. Many patients will require more than one drug to achieve blood pressure goals. For specific advice on goals and management, see published guidelines, such as those of the National High Blood Pressure Education Program's Joint National Committee on Prevention, Detection, Evaluation, and Treatment of High Blood Pressure (JNC).

Numerous antihypertensive drugs, from a variety of pharmacologic classes and with different mechanisms of action, have been shown in randomized controlled trials to reduce cardiovascular morbidity and mortality, and it can be concluded that it is blood pressure reduction, and not some other pharmacologic property of the drugs, that is largely responsible for those benefits. The largest and most consistent cardiovascular outcome benefit has been a reduction in the risk of stroke, but reductions in myocardial infarction and cardiovascular mortality also have been seen regularly.

Elevated systolic or diastolic pressure causes increased cardiovascular risk, and the absolute risk increase per mmHg is greater at higher blood pressures, so that even modest reductions of severe hypertension can provide substantial benefit. Relative risk reduction from blood pressure reduction is similar across populations with varying absolute risk, so the absolute benefit is greater in patients who are at higher risk independent of their hypertension (for example, patients with diabetes or hyperlipidemia), and such patients would be expected to benefit from more aggressive treatment to a lower blood pressure goal.

Some antihypertensive drugs have smaller blood pressure effects (as monotherapy) in black patients, and many antihypertensive drugs have additional approved indications and effects (e.g., on angina, heart failure, or diabetic kidney disease). These considerations may guide selection of therapy.

2 DOSAGE AND ADMINISTRATION

THE CONTENTS OF THE Verapamil Hydrochloride Extended-release Capsules (PM) CAPSULE SHOULD NOT BE CRUSHED OR CHEWED. Verapamil Hydrochloride Extended-release Capsules (PM) CAPSULES ARE TO BE SWALLOWED WHOLE OR THE ENTIRE CONTENTS OF THE CAPSULE SPRINKLED ONTO APPLESAUCE.

2.1 Essential Hypertension

Administer Verapamil Hydrochloride Extended-release Capsules (PM) once daily at bedtime. Clinical trials studied doses of 100 mg, 200 mg, 300 mg, and 400 mg. The usual daily dose of extended-release Verapamil Hydrochloride Extended-release Capsules (PM) in clinical trials has been 200 mg given by mouth once daily at bedtime. In rare instances, initial doses of 100 mg a day may be warranted in patients who have an increased response to verapamil [e.g. patients with impaired renal function, impaired hepatic function, elderly, low-weight patients, etc. (see Use in Specific Populations (8.5, 8.6, 8.7))]. Base upward titration on therapeutic efficacy and safety evaluated approximately 24 hours after dosing. The antihypertensive effects of Verapamil Hydrochloride Extended-release Capsules (PM) are evident within the first week of therapy.

If an adequate response is not obtained with 200 mg of Verapamil Hydrochloride Extended-release Capsules (PM), the dose may be titrated upward in the following manner:

a) 300 mg each evening b) 400 mg each evening (2 × 200 mg)

When Verapamil Hydrochloride Extended-release Capsules (PM) is administered at bedtime, office evaluation of blood pressure during morning and early afternoon hours is essentially a measure of peak effect. The usual evaluation of trough effect, which sometimes might be needed to evaluate the appropriateness of any given dose of Verapamil Hydrochloride Extended-release Capsules (PM), would be just prior to bedtime.

2.2 Sprinkling the Capsule Contents on Food

Verapamil Hydrochloride Extended-release Capsules (PM) capsules may also be administered by carefully opening the capsule and sprinkling the pellets onto one tablespoonful of applesauce. Swallow the applesauce immediately without chewing and follow with a glass of cool water to ensure complete swallowing of the pellets. The applesauce used should not be hot and it should be soft enough to be swallowed without chewing. Use any pellet/applesauce mixture immediately and do not store for future use. Absorption of the pellets sprinkled onto other foods has not been tested. This method of administration may be beneficial for patients who have difficulty swallowing whole capsules. Subdividing the contents of a Verapamil Hydrochloride Extended-release Capsules (PM) capsule is not recommended.

3 DOSAGE FORMS AND STRENGTHS

Extended-release capsules controlled onset: 100 mg, 200 mg, and 300 mg.

100 mg: white opaque cap and amethyst body imprinted KU/485 100 mg.

200 mg: amethyst opaque cap and amethyst body imprinted KU/486 200 mg.

300 mg: lavender opaque cap and amethyst body imprinted KU/487 300 mg.

4 CONTRAINDICATIONS

Verapamil is contraindicated in:

- Severe left ventricular dysfunction [see Warnings and Precautions (5.1)].
- Hypotension (less than 90 mm Hg systolic pressure) or cardiogenic shock.
- Sick sinus syndrome (except in patients with a functioning artificial ventricular pacemaker).
- Second- or third-degree AV block (except in patients with a functioning artificial ventricular pacemaker).
- Patients with atrial flutter or atrial fibrillation and an accessory bypass tract (e.g., Wolff-Parkinson-White, Lown-Ganong-Levine syndromes) [see Warnings and Precautions (5.4)].

5 WARNINGS AND PRECAUTIONS

5.1 Heart Failure

Verapamil has a negative inotropic effect which, in most patients, is compensated by its afterload reduction (decreased systemic vascular resistance) properties without a net impairment of ventricular performance. In previous clinical experience with 4,954 patients primarily with immediate-release verapamil, 87 (1.8%) developed congestive heart failure or pulmonary edema. Avoid verapamil in patients with severe left ventricular dysfunction (e.g., ejection fraction less than 30% or moderate to severe symptoms of cardiac failure) and in patients with any degree of ventricular dysfunction if they are receiving a beta-adrenergic blocker [see Drug Interactions (7.4)]. Control patients with milder ventricular dysfunction, if possible, with optimum doses of digitalis and/or diuretics before verapamil treatment is started [see Drug Interactions (7.5)].

5.2 Hypotension

Occasionally, the pharmacologic action of verapamil may produce a decrease in blood pressure below normal levels which may result in dizziness or symptomatic hypotension. In hypertensive patients, decreases in blood pressure below normal are unusual. The incidence of hypotension observed in 4,954 patients enrolled in clinical trials of other verapamil formulations was 2.5% [see Adverse Reactions (6.1)]. In clinical studies of Verapamil Hydrochloride Extended-release Capsules (PM), 1.7% of the patients developed significant hypotension. Tilt table testing (60 degrees) was not able to induce orthostatic hypotension.

5.3 Elevated Liver Enzymes

Elevations of transaminases with and without concomitant elevations in alkaline phosphatase and bilirubin have been reported. Such elevations have sometimes been transient and may disappear even in the face of continued verapamil treatment.

Several cases of hepatocellular injury related to verapamil have been proven by rechallenge; half of these had clinical symptoms (malaise, fever, and/or right upper quadrant pain) in addition to elevations of SGOT, SGPT, and alkaline phosphatase. Periodic monitoring of liver function in patients receiving verapamil is therefore prudent.

5.4 Accessory Bypass Tract (Wolff-Parkinson-White or Lown-Ganong-Levine)

Some patients with paroxysmal and/or chronic atrial flutter or atrial fibrillation and a coexisting accessory AV pathway have developed increased antegrade conduction across the accessory pathway bypassing the AV node, producing a very rapid ventricular response or ventricular fibrillation after receiving intravenous verapamil (or digitalis). Although a risk of this occurring with oral verapamil has not been established, such patients receiving oral verapamil may be at risk and its use in these patients is contraindicated [see Contraindications (4)]. Treatment is usually DC-cardioversion. Cardioversion has been used safely and effectively after oral verapamil.

5.5 Atrioventricular Block

The effect of verapamil on AV conduction and the SA node may lead to asymptomatic first-degree AV block and transient bradycardia, sometimes accompanied by nodal escape rhythms. PR interval prolongation is correlated with verapamil plasma concentrations, especially during the early titration phase of therapy. Higher degrees of AV block, however, were infrequently (0.8%) observed in previous verapamil clinical trials [see Adverse Reactions (6.1)].

Marked first-degree block or progressive development to second- or third-degree AV block requires a reduction in dosage or, in rare instances, discontinuation of verapamil and institution of appropriate therapy depending upon the clinical situation.

5.6 Patients with Hypertrophic Cardiomyopathy

In 120 patients with hypertrophic cardiomyopathy, idiopathic hypertrophic subaortic stenosis (IHSS) (most of them refractory or intolerant to propranolol) who received therapy with verapamil at doses up to 720 mg/day, a variety of serious adverse effects were seen. Three patients died in pulmonary edema; all had severe left ventricular outflow obstruction and a history of left ventricular dysfunction. Eight other patients had pulmonary edema and/or severe hypotension; abnormally high (over 20 mm Hg) pulmonary capillary wedge pressure and a marked left ventricular outflow obstruction were present in most of these patients. Concomitant administration of quinidine [see Drug Interactions (7.10)] preceded the severe hypotension in 3 of the 8 patients (2 of whom developed pulmonary edema). Sinus bradycardia occurred in 11% of the patients, second-degree AV block in 4% and sinus arrest in 2% [see Adverse Reactions (6)]. It must be appreciated that this group of patients had a serious disease with a high mortality rate. Most adverse effects responded well to dose reduction and only rarely did verapamil have to be discontinued.

6 ADVERSE REACTIONS

6.1 Clinical Trials Experience

Because clinical trials are conducted under widely varying conditions, adverse reaction rates observed in the clinical trials of a drug cannot be directly compared to rates in the clinical trials of another drug and may not reflect the rates observed in practice. The adverse reaction information from clinical trials does, however, provide a basis for identifying the adverse events that appear to be related to drug use and for approximating rates.

Serious adverse reactions are uncommon when verapamil therapy is initiated with upward dose titration within the recommended single and total daily dose. See Warnings and Precautions (5.1, 5.2, 5.3, 5.4, 5.5) for discussion of heart failure, hypotension, elevated liver enzymes, AV block, and rapid ventricular response. Reversible (upon discontinuation of verapamil) non-obstructive, paralytic ileus has been infrequently reported in association with the use of verapamil.

The following reactions (Table 1) to orally administered Verapamil Hydrochloride Extended-release Capsules (PM) occurred at rates of 2.0% or greater or occurred at lower rates but appeared to be drug-related in clinical trials in hypertension.

Table 1. Adverse Events Occurring in ≥ 2% of Verapamil Hydrochloride Extended-release Capsules (PM) Patients in Placebo- Controlled Clinical Trials
 | All Doses Studied N = 297 % | Placebo N = 116 % |  | All Doses Studied N = 297 % | Placebo N = 116 %
Headache | 12.1 | 11.2 | Dyspepsia | 2.7 | 1.7
Infection | 12.1 [Infection, primarily upper respiratory infection (URI) and unrelated to study medication. Constipation was typically mild and easily manageable. At the usual once-daily dose of 200 mg, the observed incidence of constipation was 3.9%.] | 6.9 | Rhinitis | 2.7 | 2.6
Constipation | 8.8 | 0.9 | Diarrhea | 2.4 | 1.7
Flu Syndrome | 3.7 | 2.6 | Pain | 2.4 | 1.7
Peripheral edema | 3.7 | 0.9 | Edema | 1.7 | 0.0
Dizziness | 3.0 | 0.9 | Nausea | 1.7 | 0.0
Pharyngitis | 3.0 | 2.6 | Accidental Injury | 1.5 | 0.0
Sinusitis | 3.0 | 2.6

In previous experience with other formulations of verapamil (N=4,954) the following reactions (Table 2) have occurred at rates greater than 1.0% or occurred at lower rates but appeared clearly drug related in clinical trials in 4,954 patients.

Table 2. Adverse Events Occurring in >1% (or lower rates and clearly drug related) of Patients with Other Verapamil Formulations
Constipation | 7.3% | Fatigue | 1.7%
Dizziness | 3.3% | Bradycardia (HR<50/min) | 1.4%
Nausea | 2.7% | Rash | 1.2%
Hypotension | 2.5% | AV block (total 1°, 2°, 3°) | 1.2%
Headache | 2.2% | AV block (2° and 3°) | 0.8%
Edema | 1.9% | Flushing | 0.6%
CHF/Pulmonary Edema | 1.8%

In clinical trials related to the control of ventricular response in patients taking digoxin who had atrial fibrillation or atrial flutter, ventricular rate below 50/min at rest occurred in 15% of patients and asymptomatic hypotension occurred in 5% of patients.

6.2 Open Trials / Postmarketing Experience

The following reactions, reported with orally administered verapamil in 2.0% or less of patients, occurred under conditions (open verapamil trials, postmarketing experience [reactions added since the initial US approval of Verapamil Hydrochloride Extended-release Capsules (PM) in 1998 are marked with an asterisk]) where a causal relationship is uncertain; they are listed to alert the physician to a possible relationship:

Cardiovascular: angina pectoris, atrioventricular dissociation, ECG Abnormal, chest pain, claudication, hypertension, myocardial infarction, palpitations, purpura (vasculitis), syncope.

Digestive System: diarrhea, dry mouth, elevated liver enzymes [see Warnings and Precautions (5.3)], gastrointestinal distress, gingival hyperplasia.

Hemic and Lymphatic: ecchymosis or bruising.

Nervous System: cerebrovascular accident, confusion, equilibrium disorders, extrapyramidal symptoms, insomnia, muscle cramps, paresthesia, psychotic symptoms, shakiness, somnolence.

Respiratory: dyspnea.

Skin: arthralgia and rash, exanthema, hair loss, hyperkeratosis, macules, sweating, urticaria, Stevens-Johnson syndrome, erythema multiforme.

Special Senses: blurred vision, tinnitus.

Urogenital: gynecomastia, galactorrhea/hyperprolactinemia, impotence, increased urination, spotty menstruation.

Other: allergy aggravated, asthenia.

6.3 Treatment of Acute Cardiovascular Adverse Reactions

The frequency of cardiovascular adverse reactions that require therapy is rare; hence, experience with their treatment is limited. Whenever severe hypotension or complete AV block occurs following oral administration of verapamil, apply the appropriate emergency measures immediately; e.g., intravenously administered norepinephrine bitartrate, atropine sulfate, isoproterenol HCl (all in the usual doses), or calcium gluconate (10% solution). In patients with hypertrophic cardiomyopathy, use alpha-adrenergic agents (phenylephrine HCl, metaraminol bitartrate, or methoxamine HCl) to maintain blood pressure, and isoproterenol and avoid norepinephrine. If further support is necessary, inotropic agents (dopamine HCl or dobutamine HCl) may be administered. Actual treatment and dosage depends on the severity of the clinical situation and the judgment and experience of the treating physician.

7 DRUG INTERACTIONS

7.1 CYP3A4 Inhibitors and Inducers

In vitro metabolic studies indicate that verapamil is metabolized by cytochrome P450, CYP3A4, CYP1A2, and CYP2C. Clinically significant interactions have been reported with inhibitors of CYP3A4 (e.g., erythromycin, ritonavir) causing elevation of plasma levels of verapamil. Hypotension, bradyarrhythmias, and lactic acidosis have been observed in patients receiving concurrent telithromycin, an antibiotic in the ketolide class of antibiotics. Inducers of CYP3A4 (e.g., rifampin) have caused a lowering of plasma levels of verapamil.

Ivabradine

Concurrent use of verapamil increases exposure to ivabradine and may exacerbate bradycardia and conductions disturbances. Avoid concomitant use of ivabradine and verapamil.

7.2 HMG-CoA Reductase Inhibitors

The use of HMG-CoA reductase inhibitors that are CYP3A4 substrates in combination with verapamil has been associated with reports of myopathy/rhabdomyolysis.

Co-administration of multiple doses of 10 mg of verapamil with 80 mg simvastatin resulted in exposure to simvastatin 2.5-fold that following simvastatin alone. Limit the dose of simvastatin in patients on verapamil to 10 mg daily. Limit the daily dose of lovastatin to 40 mg. Lower starting and maintenance doses of other CYP3A4 substrates (e.g., atorvastatin) may be required as verapamil may increase the plasma concentration of these drugs.

7.3 Grapefruit Juice

Grapefruit juice may significantly increase concentrations of verapamil. Grapefruit juice given to nine healthy volunteers increased S- and R- verapamil AUC 0-12 by 36% and 28%, respectively. Steady state Cmax and Cmin of S-verapamil increased by 57% and 16.7%, respectively with grapefruit juice compared to control. Similarly, Cmax and Cmin of R-verapamil increased by 40% and 13%, respectively. Grapefruit juice did not affect half-life, nor was there a significant change in AUC 0-12 ratio R/S compared to control. Grapefruit juice did not cause a significant difference in the pharmacokinetics of norverapamil. This increase in verapamil plasma concentration is not expected to have any clinical consequences.

7.4 Beta Blockers

Concomitant therapy with beta-adrenergic blockers and verapamil may result in additive negative effects on heart rate, atrioventricular conduction, and/or cardiac contractility. The combination of extended-release verapamil and beta-adrenergic blocking agents has not been studied. However, there have been reports of excess bradycardia and AV block, including complete heart block, when the combination has been used for the treatment of hypertension. For hypertensive patients, the risk of combined therapy may outweigh the potential benefits. The combination should be used only with caution and close monitoring. Asymptomatic bradycardia (36 beats/min) with a wandering atrial pacemaker has been observed in a patient receiving concomitant timolol (a beta-adrenergic blocker) eyedrops and oral verapamil.

A decrease in metoprolol and propranolol clearance has been observed when either drug is administered concomitantly with verapamil. A variable effect has been seen when verapamil and atenolol were given together.

7.5 Digitalis

Consider reducing digoxin dose when verapamil and digoxin are to be given together. Monitor digoxin level periodically during therapy. Chronic verapamil treatment can increase serum digoxin levels by 50% to 75% during the first week of therapy, and this can result in digitalis toxicity. In patients with hepatic cirrhosis the influence of verapamil on digoxin pharmacokinetics is magnified. Verapamil may reduce total body clearance and extrarenal clearance of digoxin by 27% and 29%, respectively. If digoxin toxicity is suspected, suspend or discontinue digoxin therapy.

In previous clinical trials with other verapamil formulations related to the control of ventricular response in patients taking digoxin who had atrial fibrillation or atrial flutter, ventricular rates below 50/min at rest occurred in 15% of patients, and asymptomatic hypotension occurred in 5% of patients.

7.6 Alcohol

Verapamil has been found to significantly inhibit ethanol elimination resulting in elevated blood ethanol concentrations that may prolong the intoxicating effects of alcohol.

7.7 Clonidine

Sinus bradycardia resulting in hospitalization and pacemaker insertion has been reported in association with the use of clonidine concurrently with verapamil. Monitor heart rate in patients receiving concomitant verapamil and clonidine.

7.8 Telithromycin

Hypotension and bradyarrhythmias have been observed in patients receiving concurrent telithromycin, an antibiotic in the ketolide class of antibiotics.

7.9 Antineoplastic Agents

Verapamil can increase doxorubicin levels. The absorption of verapamil can be reduced by the cyclophosphamide, oncovin, procarbazine, prednisone (COPP) and the vindesine, adriamycin, cisplatin (VAC) cytotoxic drug regimens. Concomitant administration of R verapamil can decrease the clearance of paclitaxel.

7.10 Quinidine

In a small number of patients with hypertrophic cardiomyopathy, concomitant use of verapamil and quinidine resulted in significant hypotension. Until further data are obtained, avoid combined therapy of verapamil and quinidine in patients with hypertrophic cardiomyopathy.

The electrophysiological effects of quinidine and verapamil on AV conduction were studied in 8 patients. Verapamil significantly counteracted the effects of quinidine on AV conduction. There has been a report of increased quinidine levels during verapamil therapy.

7.11 Aspirin

In a few reported cases, coadministration of verapamil with aspirin has led to increased bleeding times greater than observed with aspirin alone.

7.12 Antihypertensive Agents

Verapamil administered concomitantly with oral antihypertensive agents (e.g., vasodilators, angiotensin-converting enzyme inhibitors, diuretics, beta blockers) will usually have an additive effect on lowering blood pressure. Monitor patients receiving these combinations appropriately. Concomitant use of agents that attenuate alpha-adrenergic function with verapamil may result in reduction in blood pressure that is excessive in some patients. Such an effect was observed in one study following the concomitant administration of verapamil and prazosin.

7.13 Disopyramide

Until data on possible interactions between verapamil and disopyramide are obtained, do not administer disopyramide within 48 hours before or 24 hours after verapamil administration.

7.14 Flecainide

A study in healthy volunteers showed that the concomitant administration of flecainide and verapamil may have additive effects on myocardial contractility, AV conduction, and repolarization. Concomitant therapy with flecainide and verapamil may result in additive negative inotropic effect and prolongation of atrioventricular conduction.

7.15 Carbamazepine

Verapamil therapy may increase carbamazepine concentrations during combined therapy. This may produce carbamazepine side effects such as diplopia, headache, ataxia, or dizziness.

7.16 Cyclosporine

Verapamil therapy may increase serum levels of cyclosporine.

7.17 Lithium

Increased sensitivity to the effects of lithium (neurotoxicity) has been reported during concomitant verapamil-lithium therapy with either no change or an increase in serum lithium levels. However, the addition of verapamil has also resulted in the lowering of serum lithium levels in patients receiving chronic stable oral lithium. Patients receiving both drugs must be monitored carefully.

7.18 Inhalation Anesthetics

Animal experiments have shown that inhalation anesthetics depress cardiovascular activity by decreasing the inward movement of calcium ions. When used concomitantly, inhalation anesthetics and calcium antagonists, such as verapamil, titrate slowly to avoid excessive cardiovascular depression.

7.19 Neuromuscular Blocking Agents

Clinical data and animal studies suggest that verapamil may potentiate the activity of neuromuscular blocking agents (curare-like and depolarizing). It may be necessary to decrease the dose of verapamil and/or the dose of the neuromuscular blocking agent when the drugs are used concomitantly.

7.20 Phenobarbital

Phenobarbital therapy may increase verapamil clearance.

7.21 Rifampin

Therapy with rifampin may markedly reduce oral verapamil bioavailability.

7.22 Theophylline

Verapamil may inhibit the clearance and increase the plasma levels of theophylline.

7.23 Cimetidine

The interaction between cimetidine and chronically administered verapamil has not been studied. Variable results on clearance have been obtained in acute studies of healthy volunteers; clearance of verapamil was either reduced or unchanged.

7.24 Nitrates

Verapamil has been given concomitantly with short- and long-acting nitrates without any undesirable drug interactions. The pharmacologic profile of both drugs and the clinical experience suggest beneficial interactions.

7.25 Mammalian Target of Rapamycin (mTOR) Inhibitors

In a study of 25 healthy volunteers with co-administration of verapamil with sirolimus, whole blood sirolimus Cmax and AUC were increased 130% and 120%, respectively. Plasma S(-) verapamil Cmax and AUC were both increased 50%. Co-administration of verapamil with everolimus in 16 healthy volunteers increased the Cmax and AUC of everolimus by 130% and 250%, respectively. With concomitant use of mTOR inhibitors (e.g., sirolimus, temsirolimus, and everolimus) and verapamil, consider appropriate dose reductions of both medications.

8 USE IN SPECIFIC POPULATIONS

8.1 Pregnancy

Pregnancy Category C. Reproduction studies have been performed in rabbits and rats at oral doses up to 1.9 (15 mg/kg/day) and 7.5 (60 mg/kg/day) times the human oral daily dose, respectively, and have revealed no evidence of teratogenicity. In the rat, however, this multiple of the human dose was embryocidal and retarded fetal growth and development, probably because of adverse maternal effects reflected in reduced weight gains of the dams. This oral dose has also been shown to cause hypotension in rats. There are no adequate and well-controlled studies in pregnant women. Verapamil should be used during pregnancy only if the potential benefit justifies the potential risk to the fetus. Verapamil crosses the placental barrier and can be detected in umbilical vein blood at delivery.

8.2 Labor and Delivery

It is not known whether the use of verapamil during labor or delivery has immediate or delayed adverse effects on the fetus, or whether it prolongs the duration of labor or increases the need for forceps delivery or other obstetric intervention. Such adverse experiences have not been reported in the literature, despite a long history of use of verapamil in Europe in the treatment of cardiac side effects of beta-adrenergic agonist agents used to treat premature labor.

8.3 Nursing Mothers

Verapamil is excreted into human milk. In case studies where verapamil concentration in human milk was calculated, the nursing infant doses ranged from less than 0.01% to 0.1% of the mother's verapamil dose. Consider possible infant exposure when verapamil is administered to a nursing woman.

8.4 Pediatric Use

Safety and effectiveness in pediatric patients have not been established.

8.5 Geriatric Use

Clinical studies of Verapamil Hydrochloride Extended-release Capsules (PM) were not adequate to determine if subjects aged 65 or over respond differently from younger patients. Other reported clinical experience has not identified differences in response between the elderly and younger patients; however, greater sensitivity to Verapamil Hydrochloride Extended-release Capsules (PM) by some older individuals cannot be ruled out.

Aging may affect the pharmacokinetics of verapamil. Elimination half-life may be prolonged in the elderly [see Clinical Pharmacology (12.3)].

Verapamil is highly metabolized by the liver, and about 70% of the administered dose is excreted as metabolites in the urine. Clinical circumstances, some of which may be more common in the elderly, such as hepatic or renal impairment, should be considered [see Use in Specific Populations (8.6, 8.7)]. In general, lower initial doses of Verapamil Hydrochloride Extended-release Capsules (PM) may be warranted in the elderly [see Dosage and Administration (2.1)].

8.6 Impaired Hepatic Function

Since verapamil is highly metabolized by the liver, consider lower dosages and closely monitor responses to the drug in patients with impaired hepatic function. Severe liver dysfunction prolongs the elimination half-life of immediate-release verapamil to about 14 to 16 hours; hence, approximately 30% of the dose given to patients with normal liver function should be administered to these patients. Monitor for abnormal prolongation of the PR interval or other signs of excessive pharmacologic effects [see Overdosage (10)].

8.7 Impaired Renal Function

70% of an administered dose of verapamil is excreted as metabolites in the urine. Until further data are available, monitor these patients for abnormal prolongation of the PR interval or other signs of overdosage [see Overdosage (10)].

8.8 Attenuated (decreased) Neuromuscular Transmission

It has been reported that verapamil decreases neuromuscular transmission in patients with Duchenne's muscular dystrophy, and that verapamil prolongs recovery from the neuromuscular blocking agent vecuronium and causes a worsening of myasthenia gravis. It may be necessary to decrease the dosage of verapamil when it is administered to patients with attenuated neuromuscular transmission.

10 OVERDOSAGE

There is no specific antidote for verapamil overdosage; treatment is supportive. Delayed pharmacodynamic consequences may occur with sustained-release formulations, and observe patients for at least 48 hours, preferably under continuous hospital care. Reported effects include hypotension, bradycardia, cardiac conduction defects, arrhythmias, hyperglycemia, and decreased mental status. In addition, there have been literature reports of noncardiogenic pulmonary edema in patients taking large overdoses of verapamil (up to approximately 9 g).

In acute overdosage, consider gastrointestinal decontamination with cathartics and whole bowel irrigation. Calcium, inotropes (i.e., isoproterenol HCl, dopamine HCl, and glucagon), atropine sulfate, vasopressors (i.e., norepinephrine, and epinephrine), and cardiac pacing have been used with variable results to reverse hypotension and myocardial depression. In a few reported cases, overdose with calcium channel blockers that was initially refractory to atropine became more responsive to this treatment when the patients received large doses (close to 1 gram/hour for more than 24 hours) of calcium chloride.

Calcium chloride is preferred to calcium gluconate since it provides 3 times more calcium per volume. Asystole should be handled by the usual measures including cardiopulmonary resuscitation. Verapamil cannot be removed by hemodialysis.

11 DESCRIPTION

Verapamil Hydrochloride Extended-release Capsules (PM) is a calcium ion influx inhibitor (slow channel blocker or calcium ion antagonist). Verapamil Hydrochloride Extended-release Capsules (PM) is available for oral administration as a 100 mg hard gelatin capsule (white opaque cap/amethyst body), a 200 mg hard gelatin capsule (amethyst opaque cap/amethyst body), and as a 300 mg hard gelatin capsule (lavender opaque cap/amethyst body). Verapamil is administered as a racemic mixture of the R and S enantiomers.

The structural formulae of the verapamil HCl enantiomers are:

C27H38N2O4∙HCl M.W.=491.07

Chemical name: Benzeneacetonitrile, α-[3-[[2-(3,4-dimethoxyphenyl)ethyl]methylamino]propyl]- 3,4-dimethoxy-α-(1-methylethyl)-, monohydrochloride,(±)-.

Verapamil HCl is an almost white, crystalline powder, practically free of odor, with a bitter taste. It is soluble in water, chloroform and methanol. Verapamil HCl is not structurally related to other cardioactive drugs.

In addition to verapamil HCl the Verapamil Hydrochloride Extended-release Capsules (PM) capsule contains the following inactive ingredients: D&C Red #28, FD & C Blue #1, FD&C red #40, fumaric acid, gelatin, povidone, shellac, silicon dioxide, sodium lauryl sulfate, starch, sugar spheres, talc, and titanium dioxide.

System Components and Performance: Verapamil Hydrochloride Extended-release Capsules (PM) uses the proprietary CODAS® (Chronotherapeutic Oral Drug Absorption System) technology, which is designed for bedtime dosing, incorporating a 4 to 5-hour delay in drug delivery. The controlled-onset delivery system results in a maximum plasma concentration (Cmax) of verapamil in the morning hours. These pellet filled capsules provide for extended-release of the drug in the gastrointestinal tract. The Verapamil Hydrochloride Extended-release Capsules (PM) formulation has been designed to initiate the release of verapamil 4-5 hours after ingestion. This delay is introduced by the level of non-enteric release-controlling polymer applied to drug loaded beads. The release-controlling polymer is a combination of water soluble and water insoluble polymers. As water from the gastrointestinal tract comes into contact with the polymer coated beads, the water soluble polymer slowly dissolves and the drug diffuses through the resulting pores in the coating. The water insoluble polymer continues to act as a barrier, maintaining the controlled release of the drug. The rate of release is essentially independent of pH, posture and food. Multiparticulate systems such as Verapamil Hydrochloride Extended-release Capsules (PM) have been shown to be independent of gastrointestinal motility.

12 CLINICAL PHARMACOLOGY

12.1 Mechanism of Action

Verapamil is a calcium ion influx inhibitor (L-type calcium channel blocker or calcium channel antagonist). Verapamil exerts its pharmacologic effects by selectively inhibiting the transmembrane influx of ionic calcium into arterial smooth muscle as well as in conductile and contractile myocardial cells without altering serum calcium concentrations. Verapamil binding is voltage-dependent with affinity increasing as the vascular smooth muscle membrane potential is reduced. In addition, verapamil binding is frequency dependent and apparent affinity increases with increased frequency of depolarizing stimulus.

The L-type calcium channel is an oligomeric structure consisting of five putative subunits designated alpha-1, alpha-2, beta, tau, and epsilon. Biochemical evidence points to separate binding sites for 1,4-dihydropyridines, phenylalkylamines, and the benzothiazepines (all located on the alpha-1 subunit). Although they share a similar mechanism of action, calcium channel blockers represent three heterogeneous categories of drugs with differing vascular-cardiac selectivity ratios.

12.2 Pharmacodynamics

Essential Hypertension: Verapamil produces its antihypertensive effect by a combination of vascular and cardiac effects. It acts as a vasodilator with selectivity for the arterial portion of the peripheral vasculature. As a result the systemic vascular resistance is reduced and usually without orthostatic hypotension or reflex tachycardia. Bradycardia (rate less than 50 beats/min) is uncommon. During isometric or dynamic exercise verapamil does not alter systolic cardiac function in patients with normal ventricular function.

Verapamil does not alter total serum calcium levels. However, one report has suggested that calcium levels above the normal range may alter the therapeutic effect of verapamil.

Verapamil regularly reduces the total systemic resistance (afterload) against which the heart works both at rest and at a given level of exercise by dilating peripheral arterioles.

Electrophysiologic Effects: Electrical activity through the AV node depends, to a significant degree, upon the transmembrane influx of extracellular calcium through the L-type (slow) channel. By decreasing the influx of calcium, verapamil prolongs the effective refractory period within the AV node and slows AV conduction in a rate-related manner.

Normal sinus rhythm is usually not affected, but in patients with sick sinus syndrome, verapamil may interfere with sinus-node impulse generation and may induce sinus arrest or sinoatrial block. Atrioventricular block can occur in patients without pre-existing conduction defects [see Warnings and Precautions (5.5)].

Verapamil does not alter the normal atrial action potential or intraventricular conduction time, but depresses amplitude, velocity of depolarization, and conduction in depressed atrial fibers. Verapamil may shorten the antegrade effective refractory period of the accessory bypass tract. Acceleration of ventricular rate and/or ventricular fibrillation has been reported in patients with atrial flutter or atrial fibrillation and a coexisting accessory AV pathway following administration of verapamil [see Warnings and Precautions (5.4)].

Verapamil has a local anesthetic action that is 1.6 times that of procaine on an equimolar basis. It is not known whether this action is important at the doses used in man.

Hemodynamics: Verapamil reduces afterload and myocardial contractility. In most patients, including those with organic cardiac disease, the negative inotropic action of verapamil is countered by reduction of afterload and cardiac index remains unchanged. During isometric or dynamic exercise, verapamil does not alter systolic cardiac function in patients with normal ventricular function. In patients with severe left ventricular dysfunction (e.g., pulmonary wedge pressure above 20 mm Hg or ejection fraction less than 30%), or in patients taking beta-adrenergic blocking agents or other cardiodepressant drugs, deterioration of ventricular function may occur [see Drug Interactions (7.4)].

Pulmonary Function: Verapamil does not induce bronchoconstriction and, hence, does not impair ventilatory function.

Verapamil has been shown to have either a neutral or relaxant effect on bronchial smooth muscle.

12.3 Pharmacokinetics

Verapamil is administered as a racemic mixture of the R and S enantiomers. The systemic concentrations of R and S enantiomers, as well as overall bioavailability, are dependent upon the route of administration and the rate and extent of release from the dosage forms. Upon oral administration, there is rapid stereoselective biotransformation during the first pass of verapamil through the portal circulation.

Absorption: In a study in 5 subjects with oral immediate-release verapamil, the systemic bioavailability was from 33% to 65% for the R enantiomer and from 13% to 34% for the S enantiomer. Following oral administration of an immediately releasing formulation every 8 hours in 24 subjects, the relative systemic availability of the S enantiomer compared to the R enantiomer was approximately 13% following a single day's administration and approximately 18% following administration to steady-state. The degree of stereoselectivity of metabolism for Verapamil Hydrochloride Extended-release Capsules (PM) was similar to that for the immediately releasing formulation. The R and S enantiomers have differing levels of pharmacologic activity. In studies in animals and humans, the S enantiomer has 8 to 20 times the activity of the R enantiomer in slowing AV conduction. In animal studies, the S enantiomer has 15 to 50 times the activity of the R enantiomer in reducing myocardial contractility in isolated blood-perfused dog papillary muscle, respectively, and twice the effect in reducing peripheral resistance. In isolated septal strip preparations from 5 patients, the S enantiomer was 8 times more potent than the R in reducing myocardial contractility. Dose escalation study data indicate that verapamil concentrations increase disproportionally to dose as measured by relative peak plasma concentrations (Cmax) or areas under the plasma concentration vs time curves (AUC).

Consumption of a high fat meal just prior to dosing in the morning had no effect on the extent of absorption and a modest effect on the rate of absorption from Verapamil Hydrochloride Extended-release Capsules (PM). The rate of absorption was not affected by whether the volunteers were supine two hours after night-time dosing or non-supine for four hours following morning dosing. Administering Verapamil Hydrochloride Extended-release Capsules (PM) in the morning increased the extent of absorption of verapamil and/or decreased the metabolism to norverapamil.

When the contents of the Verapamil Hydrochloride Extended-release Capsules (PM) capsule were administered by sprinkling onto one tablespoonful of applesauce, the rate and extent of verapamil absorption were found to be bioequivalent to the same dose when administered as an intact capsule. Similar results were observed with norverapamil.

Distribution: Although some evidence of lack of dose linearity was observed for Verapamil Hydrochloride Extended-release Capsules (PM), this non-linearity was enantiomer specific, with the R enantiomer showing the greatest degree of non-linearity.

Table 3. Pharmacokinetic Characteristics of Verapamil Enantiomers After Administration of Escalating Doses of Verapamil Hydrochloride Extended-release Capsules (PM)
 | ISOMER | 200 | 300 | 400
Dose Ratio |  | 1 | 1.5 | 2
Relative Cmax | R | 1 | 1.89 | 2.34
Relative Cmax | S | 1 | 1.88 | 2.5
Relative AUC | R | 1 | 1.67 | 2.34
Relative AUC | S | 1 | 1.35 | 2.20

Racemic verapamil is released from Verapamil Hydrochloride Extended-release Capsules (PM) by diffusion following the gradual solubilization of the water soluble polymer. The rate of solubilization of the water soluble polymer produces a lag period in drug release for approximately 4-5 hours. The drug release phase is prolonged with the peak plasma concentration (Cmax) occurring approximately 11 hours after administration. Trough concentrations occur approximately 4 hours after bedtime dosing while the patient is sleeping. Steady-state pharmacokinetics were determined in healthy volunteers. Steady-state concentration is achieved by day 5 of dosing.

In healthy volunteers, following administration of Verapamil Hydrochloride Extended-release Capsules (PM) (200 mg per day), steady-state pharmacokinetics of the R and S enantiomers of verapamil is as follows: Mean Cmax of the R isomer was 77.8 ng/ml and 16.8 ng/ml for the S isomer; AUC (0-24h) of the R isomer was 1037 ng∙h/ml and 195 ng∙h/ml for the S isomer.

In general, bioavailability of verapamil is higher and half life longer in older (>65 yrs) subjects. Lean body weight also affects its pharmacokinetics inversely. It was not possible to observe a gender difference in the clinical trials of Verapamil Hydrochloride Extended-release Capsules (PM) due to the small sample size. However, there are conflicting data in the literature suggesting that verapamil clearance decreased with age in women to a greater degree than in men.

Metabolism and Excretion: Orally administered verapamil undergoes extensive metabolism in the liver. Verapamil is metabolized by O-demethylation (25%) and N-dealkylation (40%), and is subject to pre-systemic hepatic metabolism with elimination of up to 80% of the dose. The metabolism is mediated by hepatic cytochrome P450, and animal studies have implied that the mono-oxygenase is the specific isoenzyme of the P450 family. Thirteen metabolites have been identified in urine. Norverapamil enantiomers can reach steady-state plasma concentrations approximately equal to those of the enantiomers of the parent drug. For Verapamil Hydrochloride Extended-release Capsules (PM), the norverapamil R enantiomer reached steady-state plasma concentrations similar to the verapamil R enantiomer, but the norverapamil S enantiomer concentrations were approximately twice that of the verapamil S enantiomer concentrations. The cardiovascular activity of norverapamil appears to be approximately 20% that of verapamil. Approximately 70% of an administered dose is excreted as metabolites in the urine and 16% or more in the feces within 5 days. About 3% to 4% is excreted in the urine as unchanged drug.

R verapamil is 94% bound to plasma albumin, while S verapamil is 88% bound. In addition, R verapamil is 92% and S verapamil 86% bound to alpha-1 acid glycoprotein. In patients with hepatic insufficiency, metabolism of immediate-release verapamil is delayed and elimination half-life prolonged up to 14 to 16 hours because of the extensive hepatic metabolism [see Use in Specific Populations (8.6)]. In addition, in these patients there is a reduced first pass effect, and verapamil is more bioavailable. Verapamil clearance values suggest that patients with liver dysfunction may attain therapeutic verapamil plasma concentrations with one third of the oral daily dose required for patients with normal liver function.

After four weeks of oral dosing of immediate-release verapamil (120 mg q.i.d.), verapamil and norverapamil levels were noted in the cerebrospinal fluid with estimated partition coefficient of 0.06 for verapamil and 0.04 for norverapamil.

Geriatric Use: The pharmacokinetics of verapamil GITS were studied after 5 consecutive nights of dosing 180 mg in 30 healthy young (19-43 years) versus 30 healthy elderly (65-80 years) male and female subjects. Older subjects had significantly higher mean verapamil Cmax, Cmin and AUC(0-24h) compared to younger subjects. Older subjects had mean AUCs that were approximately 1.7-2.0 times higher than those of younger subjects as well as a longer average verapamil t½ (approximately 20 hr vs 13 hr).

13 NONCLINICAL TOXICOLOGY

13.1 Carcinogenesis, Mutagenesis, Impairment of Fertility

An 18-month toxicity study in rats, at a low multiple (6-fold) of the maximum recommended human dose, and not the maximum tolerated dose, did not suggest a tumorigenic potential. There was no evidence of a carcinogenic potential of verapamil administered in the diet of rats for two years at doses of 10, 35 and 120 mg/kg/day or approximately 1.3, 4.4 and 15 times, respectively, the maximum recommended human daily dose (400 mg/day or 8 mg/kg/day).

Verapamil was not mutagenic in the Ames test in 5 test strains at 3 mg per plate, with or without metabolic activation.

Studies in female rats at daily dietary doses up to 6.9 times (55 mg/kg/day) the maximum recommended human dose did not show impaired fertility. Effects on male fertility have not been determined.

13.2 Animal Toxicology and/or Pharmacology

In chronic animal toxicology studies verapamil caused lenticular and/or suture line changes at 30 mg/kg/day or greater and frank cataracts at 62.5 mg/kg/day or greater in the beagle dog but not in the rat. Development of cataracts due to verapamil has not been reported in man.

14 CLINICAL STUDIES

Verapamil Hydrochloride Extended-release Capsules (PM) was evaluated in two placebo-controlled, parallel design, double-blind studies of patients with mild to moderate hypertension. In the clinical trials, 413 evaluable patients were randomized to either placebo, 100 mg, 200 mg, 300 mg, or 400 mg and treated for up to 8 weeks. Verapamil Hydrochloride Extended-release Capsules (PM) or placebo was given once daily between 9 pm and 11 pm (nighttime) and blood pressure changes were measured with 36-hour ambulatory blood pressure monitoring (ABPM). The results of these studies demonstrate that Verapamil Hydrochloride Extended-release Capsules (PM), at 200, 300, and 400 mg, is a consistently and significantly more effective antihypertensive agent than placebo in reducing ambulatory blood pressures. Over this dose range, the placebo-subtracted net decreases in diastolic BP at trough (averaged over 6-10 pm) were dose-related, and ranged from 3.8 to 10.0 mm Hg after 8 weeks of therapy. Although Verapamil Hydrochloride Extended-release Capsules (PM) 100 mg was not effective in reducing diastolic BP at trough when measured by ABPM, efficacy was demonstrated in reducing diastolic BP when measured manually at trough and peak and, from 6 am to 12 noon and over 24 hours when measured by ABPM [see Dosage and Administration (2.1) for titration schedule].

There were no apparent treatment differences between patient subgroups of different age (older or younger than 65 years), sex and race. For severity of hypertension, "moderate" hypertensives (mean daytime diastolic BP ≥ 105 mm Hg and ≤ 114 mm Hg) appeared to respond better than "mild" hypertensives (mean daytime diastolic BP ≥ 90 mm Hg and ≤ 104 mm Hg). However, sample size for the subgroup comparisons were limited.

16 HOW SUPPLIED/STORAGE AND HANDLING

Verapamil Hydrochloride Extended-release Capsules (PM) (verapamil hydrochloride) extended-release pellet filled capsules are supplied in three dosage strengths:

100 mg: | Two piece size 2 hard gelatin capsule, white opaque cap and amethyst body imprinted KU/485 100 mg. Product identification printed in black ink, supplied as follows: NDC 62175-485-37 Bottle of 100s
200 mg: | Two piece size 0 hard gelatin capsule, amethyst opaque cap and amethyst body imprinted KU/486 200 mg. Product identification printed in black ink, supplied as follows: NDC 62175-486-37 Bottle of 100s
300 mg: | Two piece size 00 hard gelatin capsule, lavender opaque cap and amethyst body imprinted KU/487 300 mg. Product identification printed in black ink, supplied as follows: NDC 62175-487-37 Bottle of 100s

STORAGE AND HANDLING

Store at 25°C (77°F); excursions permitted to 15-30°C (59-86°F). [See USP Controlled Room Temperature]. Protect from moisture.

Dispense in tight, light-resistant container as defined in USP.

17 PATIENT COUNSELING INFORMATION

- THE CONTENTS OF THE Verapamil Hydrochloride Extended-release Capsules (PM) CAPSULE SHOULD NOT BE CRUSHED OR CHEWED. Verapamil Hydrochloride Extended-release Capsules (PM) CAPSULES ARE TO BE SWALLOWED WHOLE OR THE ENTIRE CONTENTS OF THE CAPSULE SPRINKLED ONTO APPLESAUCE [see Dosage and Administration (2.2)].
- When the sprinkle method of administration is prescribed, explain the details of the proper technique to the patient. [See Dosage and Administration (2.2)].

Distributed by:

Lannett Company, Inc.
Philadelphia, PA 19136

Manufactured by:

Societal CDMO Gainesville, LLC
Gainesville, GA 30504, USA

CODAS® is a registered trademark of Alkermes Pharma Ireland Limited, used under license

Printed in USA

Material Code: 6002499-06 Rev. 07/2022

PRINCIPAL DISPLAY PANEL - 100 mg Capsule Bottle Label

NDC 62175- 485-37

Verapamil
Hydrochloride
Extended-release
Capsules (PM)

100 mg
Rx Only

100 Capsules

Lannett

PRINCIPAL DISPLAY PANEL - 200 mg Capsule Bottle Label

NDC 62175- 486-37

Verapamil
Hydrochloride
Extended-release
Capsules (PM)

200 mg

Rx Only
100 Capsules

Lannett

PRINCIPAL DISPLAY PANEL - 300 mg Capsule Bottle Label

NDC 62175- 487-37

Verapamil
Hydrochloride
Extended-release
Capsules (PM)

300 mg

Rx Only
100 Capsules

Lannett